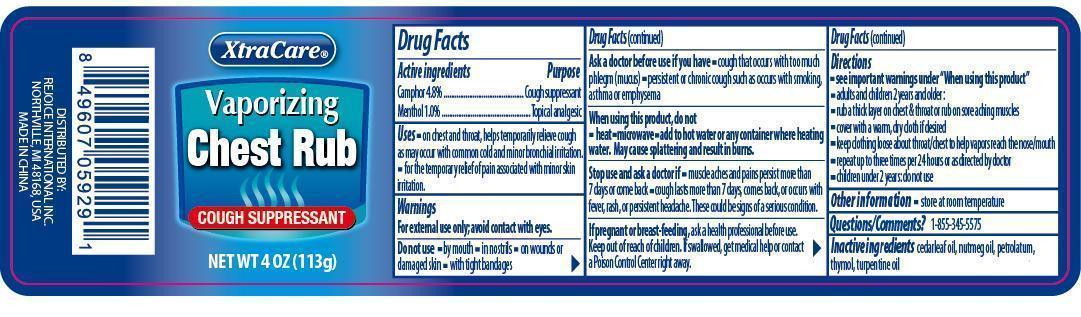 DRUG LABEL: XtraCare Vaporizing Chest Rub
NDC: 57337-051 | Form: GEL
Manufacturer: Rejoice International
Category: otc | Type: HUMAN OTC DRUG LABEL
Date: 20240228

ACTIVE INGREDIENTS: CAMPHOR (NATURAL) 5 g/113 g; MENTHOL 1 g/113 g
INACTIVE INGREDIENTS: CEDAR LEAF OIL; NUTMEG OIL; PETROLATUM; THYMOL; TURPENTINE OIL

XtraCare Vaporizing Chest Rub

Active Ingredients Purpose

Camphor 4.8% ..................................... Cough Suppressant

Menthol 1.0% ............................................ Topical Analgesic

Uses

- on chest and throat, temporarily relieves cough as may occur with common cold and minor bronchial irritation.
- for the temporary relief of pain associated with minor skin irritation.

Keep out of reach of children. If swallowed, get medical help or contact a Poison Control Center right away.

INDICATIONS AND USAGE

XtraCare® Vaporizing Chest Rub

Cough Suppressant

Net Wt 4 Oz (113 g)

Warnings

For external use only; avoid contact with eyes.

Do not use

- by mouth
- in nostrils
- on wounds or damaged skin
- with tight bandages

Ask a doctor before use if you have

- cough that occurs with too much phlegm (mucus)
- persistent or chronic cough such as occurs with smoking, asthma or emphysema

When using this product, do not

- heat
- microwave
- add to hot water or any container where heating water. May cause splattering and result in burns.

Stop use and ask a doctor if

- muscle aches and pains persist more than 7 days or come back
- cough lasts more than 7 days, comes back, or occurs with fever, rash, or persistent headache. These could be signs of a serious condition.

If pregnant or breast-feeding, ask a health professional before use.

Directions

- see important warnings under "When using this product"
- adults and children 2 years old and older:
- rub a thick layer on chest & throat or rub on sore aching muscles
- cover with a warm, dry cloth if desired
- keep clothing loose about throat chest to help vapors reach the nose/mouth
- repeat up to three times per 24 hours or as directed by doctor
- children under 2 years: do not use

Inactive Ingredients:

cedarleaf oil, nutmeg oil, petrolatum, thymol, turpentine oil

Other Information:store at room temperature

Questions/Comments?1-855-345-5575

DISTRIBUTED BY:

REJOICE INTERNATIONAL INC

NORTHVILLE, MI 48168 USA

MADE IN CHINA